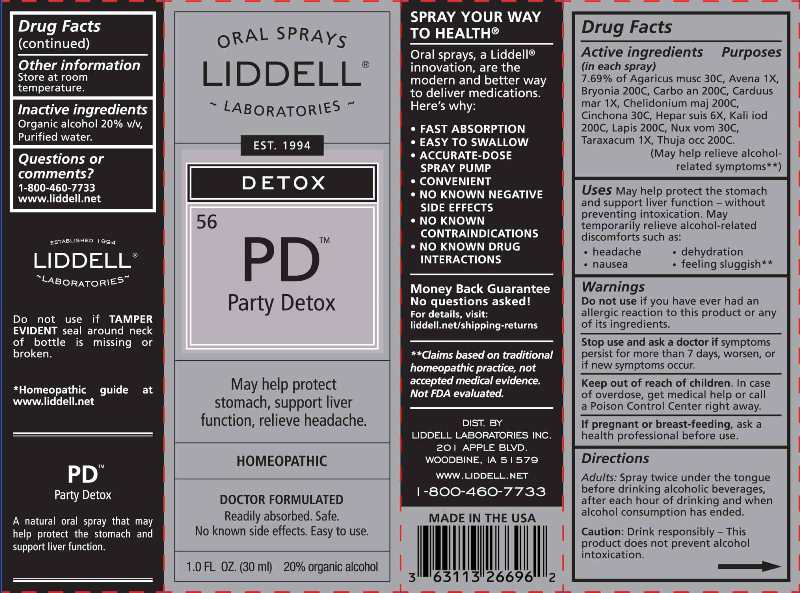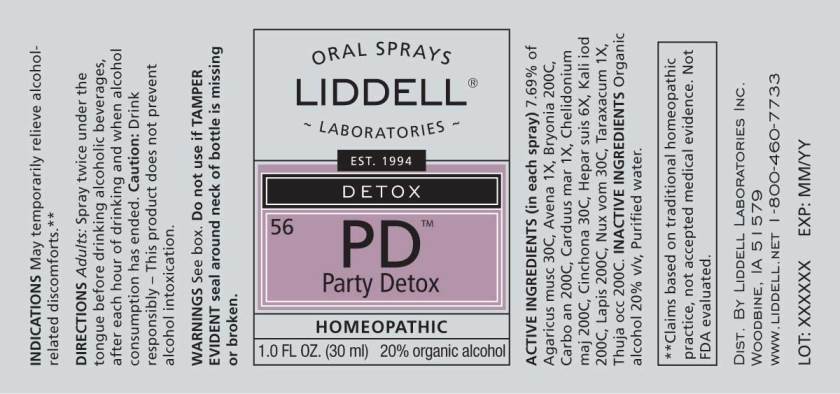 DRUG LABEL: Party Detox
NDC: 50845-0252 | Form: SPRAY
Manufacturer: Liddell Laboratories, Inc.
Category: homeopathic | Type: HUMAN OTC DRUG LABEL
Date: 20241104

ACTIVE INGREDIENTS: AMANITA MUSCARIA FRUITING BODY 30 [hp_C]/1 mL; AVENA SATIVA FLOWERING TOP 1 [hp_X]/1 mL; BRYONIA ALBA ROOT 200 [hp_C]/1 mL; CARBO ANIMALIS 200 [hp_C]/1 mL; MILK THISTLE 1 [hp_X]/1 mL; CHELIDONIUM MAJUS WHOLE 200 [hp_C]/1 mL; CINCHONA OFFICINALIS BARK 30 [hp_C]/1 mL; PORK LIVER 6 [hp_X]/1 mL; POTASSIUM IODIDE 200 [hp_C]/1 mL; CALCIUM HEXAFLUOROSILICATE 200 [hp_C]/1 mL; STRYCHNOS NUX-VOMICA SEED 30 [hp_C]/1 mL; TARAXACUM OFFICINALE 1 [hp_X]/1 mL; THUJA OCCIDENTALIS LEAFY TWIG 200 [hp_C]/1 mL
INACTIVE INGREDIENTS: WATER; ALCOHOL

DRUG FACTS:

ACTIVE INGREDIENTS:

(in each spray): 7.69% of Agaricus muscarius 30C, Avena Sativa 1X, Bryonia (Alba) 200C, Carbo Animalis 200C, Carduus Marianus 1X, Chelidonium Majus 200C, Cinchona officinalis 30C, Hepar Suis 6X, Kali Iodatum 200C, Lapis Albus 200C, Nux Vomica 30C, Taraxacum Officinale 1X, Thuja Occidentalis 200C.

USES:

May help protect the stomach and support liver function - without preventing intoxication. May temporarily relieve alcohol-related discomforts such as:

- headache

- dehydration

- nausea

- feeling sluggish**

**Claims based on traditional homeopathic practice, not accepted medical evidence. Not FDA evaluated.

WARNINGS:

Do not use if you have ever had an allergic reaction to this product or any of its ingredients.

Stop use and ask a doctor if symptoms persist for more than 7 days, worsen, or if new symptoms occur.

Keep out of reach of children. In case of overdose, get medical help or call a Poison Control Center right away.

If pregnant or breast feeding, ask a health professional before use.

Store at room temperature.

Do not use is TAMPER EVIDENT seal around neck of bottle is missing or broken.

Keep out of reach of children. In case of overdose, get medical help or call a Poison Control Center right away.

DIRECTIONS:

ADULTS: Spray twice under the tongue before drinking alcoholic beverages, after each hour of drinking and when alcohol consumption has ended.

Caution: Drink responsibly - This product does not prevent alcohol intoxication.

INDICATIONS:

May help protect the stomach and support liver function - without preventing intoxication. May temporarily relieve alcohol-related discomforts such as:

- headache

- dehydration

- nausea

- feeling sluggish**

**Claims based on traditional homeopathic practice, not accepted medical evidence. Not FDA evaluated.

INACTIVE INGREDIENTS:

Organic alcohol 20% v/v, Purified water.

QUESTIONS:

DIST. BY

LIDDELL LABORATORIES, INC.

201 APPLE BLVD.

WOODBINE, IA 51579

WWW.LIDDELL.NET

1-800-460-7733

PACKAGE DISPLAY LABEL:

ORAL SPRAYS

LIDDELL

LABORATORIES

EST. 1994

DETOX

^56 PD

Party Detox

May help protect

stomach, support liver

function, relieve headache.

HOMEOPATHIC

DOCTOR FORMULATED

Readily absorbed. Safe.

No known side effects. Easy to use.

1.0 FL OZ. (30 ml) 20% organic alcohol